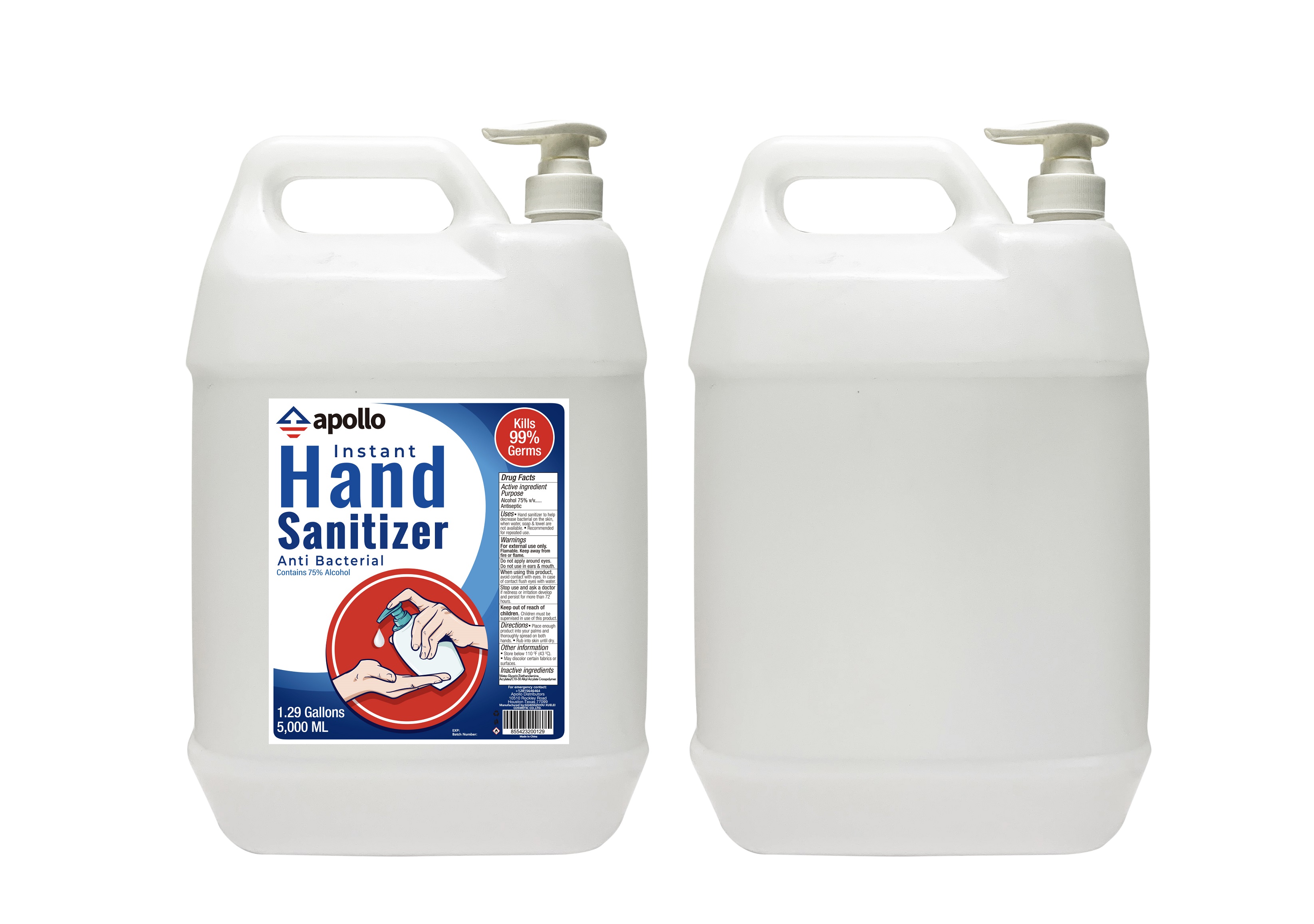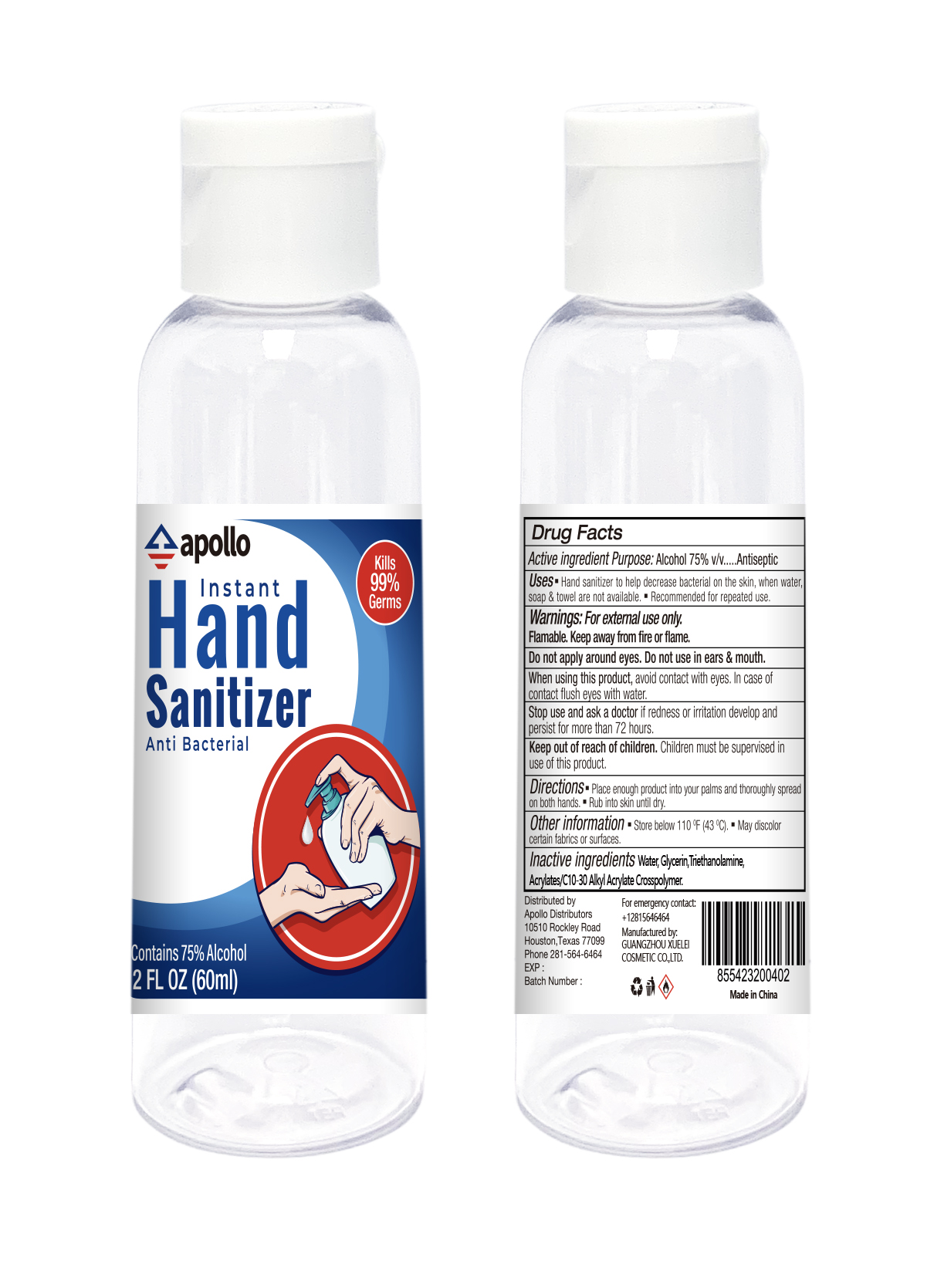 DRUG LABEL: apollo Instant Hand Sanitizer
NDC: 78303-001 | Form: GEL
Manufacturer: Sbu Group L.P.
Category: otc | Type: HUMAN OTC DRUG LABEL
Date: 20211108

ACTIVE INGREDIENTS: ALCOHOL 75 mL/100 mL
INACTIVE INGREDIENTS: TROLAMINE; CARBOMER COPOLYMER TYPE B (ALLYL PENTAERYTHRITOL CROSSLINKED); WATER; GLYCERIN

apollo Instant Hand Sanitizer

Active ingredient

Alcohol 75%v/v

Purpose

Antiseptic

Uses:

Hand sanitizer to help decrease bacterial on the skin, when water, soap& towel are not available.

Recommended for repeated use.

Warnings

For external use only. Flammable. Keep away from fire or flame.

Do not apply around eyes. Do not use in ears & mouth.

When using this product,

Avoid contact with eyes. In case of contact flush eyes with water.

Stop use and ask a doctor

If redness or irritation develop and persist for more than 72 hours

Keep out of reach of children.

Children must be supervised in use of this product.

Directions

Place enough product into your palms and thoroughly spread on both hands.

Rub into skin until dry.

Other information

Store below 110℉（43℃）

May discolor certain fabrics or surfaces.

Inactive ingredients

Water, Glycerin, Triethanolamine, Acrylates/C10-30 Alkyl Acrylate Crosspolymer.

Package Label

apollo

Instant Hand Sanitizer

Anti Bacterial

Contains 75 % Alcohol

2 FL OZ (60ml)

Kills 99% Germs

NDC: 78303-001-01

Package Label

apollo

Instant Hand Sanitizer

Anti Bacterial

Contains 75 % Alcohol

1.29 Gallons

5,000 ML

Kills 99% Germs

NDC: 78303-001-02